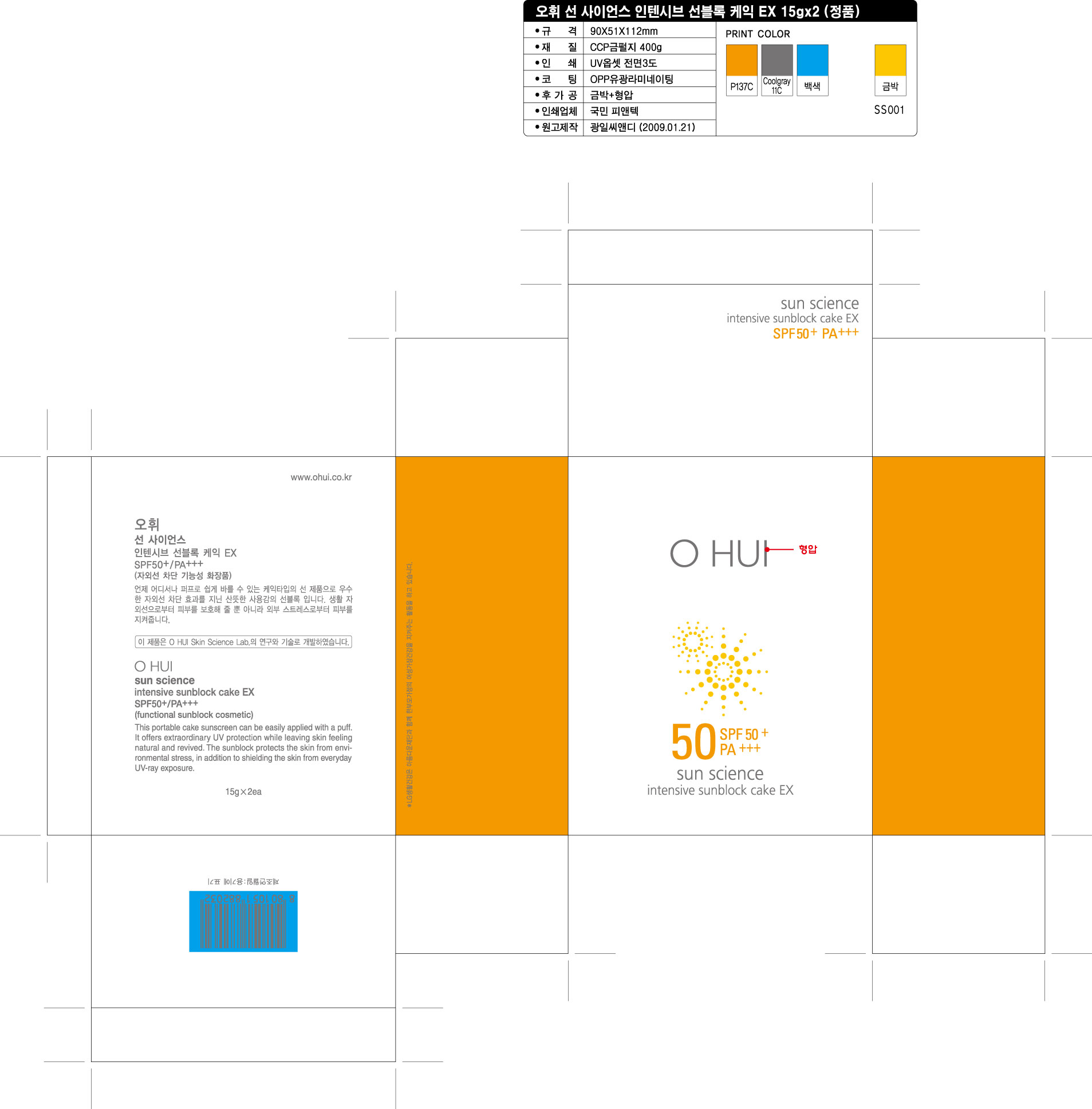 DRUG LABEL: OHUI Sun Science intensive sunblock cake EX
NDC: 53208-473 | Form: CREAM
Manufacturer: LG Household and Healthcare, Inc.
Category: otc | Type: HUMAN OTC DRUG LABEL
Date: 20100716

ACTIVE INGREDIENTS: ZINC OXIDE 10.528 g/100 g; OCTINOXATE 7 g/100 g; TITANIUM DIOXIDE 4 g/100 g; BEMOTRIZINOL  1.5 g/100 g
INACTIVE INGREDIENTS: DIMETHICONE; CYCLOMETHICONE; CYCLOMETHICONE; METHYLPARABEN

Drug Facts

ACTIVE INGREDIENT

ZINC OXIDE 10.528g/100g

OCTINOXATE 7g/100g

TITANIUM DIOXIDE 4g/100g

BEMOTRIZINOL 1.5g/100g

WARNINGS AND PRECAUTIONS

For external use only.

Keep out of reach of children

If swallowed, get medical help or contact a Poison Control Center right away.

STOP USE

Stop use if a rash or irritation develops and lasts.

WHEN USING

Keep out of eyes. Rinse with water to remove.

PACKAGE LABEL

OHUI

Sun Science

Intensive Sunblock Cake EX